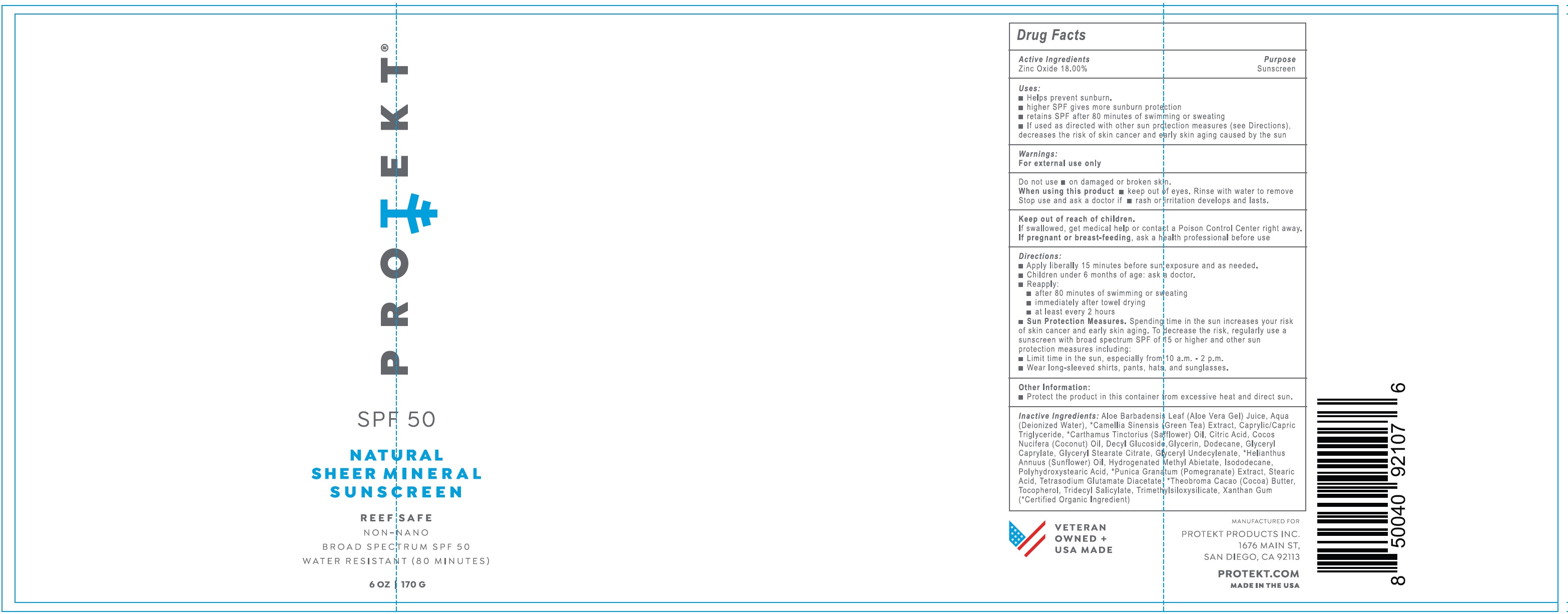 DRUG LABEL: PROTEKT SPF-50 Sheer Mineral Sunscreen
NDC: 82912-323 | Form: CREAM
Manufacturer: Protekt Products, Inc.
Category: otc | Type: HUMAN OTC DRUG LABEL
Date: 20231111

ACTIVE INGREDIENTS: ZINC OXIDE 180 mg/1 g
INACTIVE INGREDIENTS: ALOE VERA LEAF; WATER; GREEN TEA LEAF; MEDIUM-CHAIN TRIGLYCERIDES; SAFFLOWER; CITRIC ACID MONOHYDRATE; COCONUT OIL; DECYL GLUCOSIDE; GLYCERIN; DODECANE; GLYCERYL CAPRYLATE; GLYCERYL STEARATE CITRATE; HELIANTHUS ANNUUS FLOWERING TOP; HYDROGENATED METHYL ABIETATE; ISODODECANE; PUNICA GRANATUM ROOT BARK; STEARIC ACID; TETRASODIUM GLUTAMATE DIACETATE; COCOA; TOCOPHEROL; TRIDECYL SALICYLATE; XANTHAN GUM

PROTEKT SPF-50 Sheer Mineral Sunscreen

Active Ingredients

Zinc Oxide 18.00%

Purpose

Sunscreen

Uses:

- Helps prevent sunburn.
- higher SPF gives more sunburn protection
- retains SPF after 80 minutes of swimming or sweating
- If used as directed with other sun protection measures (see Directions), decreases the risk of skin cancer and early skin aging caused by the sun

Warnings:

For external use only

Do not use

- on damaged or broken skin.

When using this product

- keep out of eyes. Rinse with water to remove

Stop use and ask a doctor if

- rash or irritation develops and lasts.

Keep out of reach of children.

If swallowed, get medical help or contact a Poison Control Center right away.

If pregnant or breast-feeding,

ask a health professional before use

Directions:

- Apply liberally 15 minutes before sun exposure and as needed.
- Children under 6 months of age: ask a doctor.
- Reapply:
- after 80 minutes of swimming or sweating
- immediately after towel drying
- at least every 2 hours
- Spending time in the sun increases your risk of skin cancer and early skin aging. To decrease the risk, regularly use a sunscreen with broad spectrum SPF of 15 or higher and other sun protection measures including: Sun Protection Measures.
- Limit time in the sun, especially from 10 a.m. - 2 p.m.
- Wear long-sleeved shirts, pants, hats, and sunglasses.

Other Information:

- Protect the product in this container from excessive heat and direct sun.

Inactive Ingredients:

*Aloe Barbadensis Leaf (Aloe Vera Gel) Juice, Aqua (Deionized Water), *Camellia Sinensis (Green Tea) Extract, Caprylic/Capric Triglyceride, *Carthamus Tinctorius (Safflower) Oil, Citric Acid, Cocos Nucifera (Coconut) Oil, Decyl Glucoside, Glycerin, Dodecane, Glyceryl Caprylate, Glyceryl Stearate Citrate, Glyceryl Undecylenate, *Helianthus Annuus (Sunflower) Oil, Hydrogenated Methyl Abietate, Isododecane, Polyhydroxystearic Acid, *Punica Granatum (Pomegranate) Extract, Stearic Acid, Tetrasodium Glutamate Diacetate, *Theobroma Cacao (Cocoa) Butter, Tocopherol, Tridecyl Salicylate, Trimethylsiloxysilicate, Xanthan Gum

(*Certified Organic Ingredient)